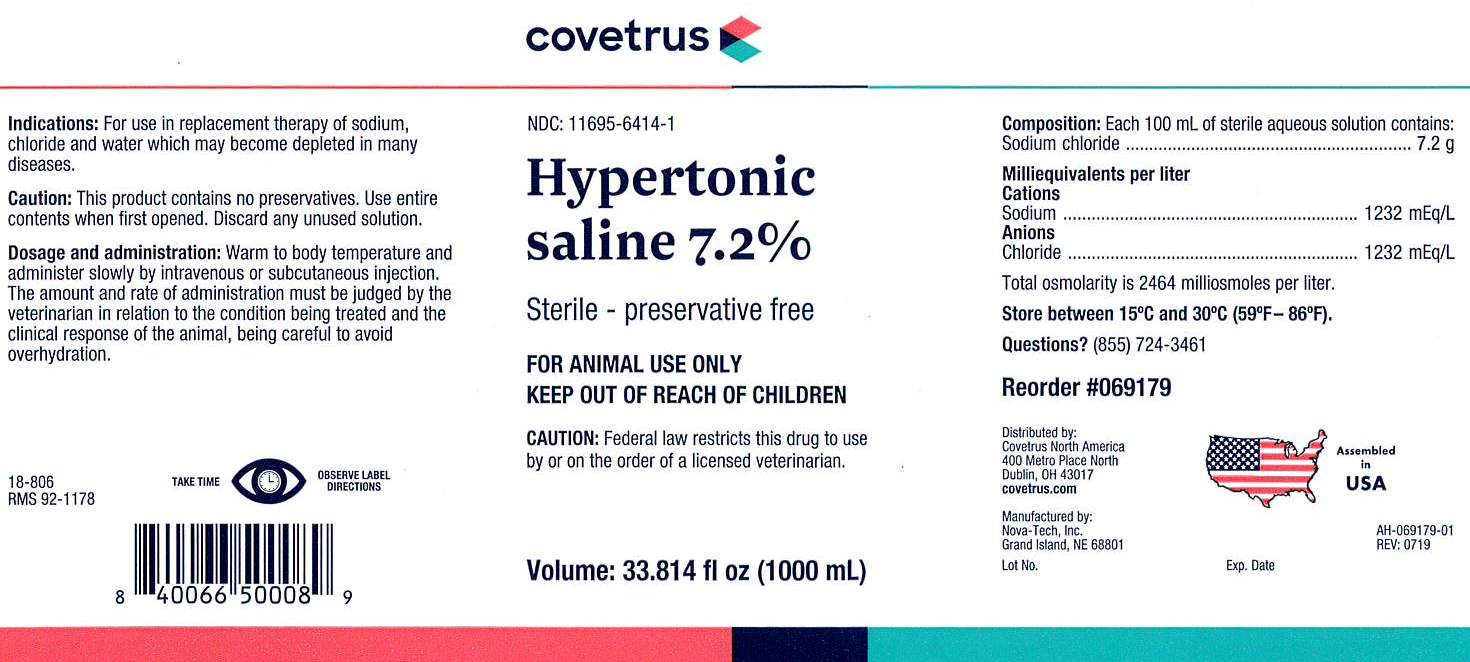 DRUG LABEL: Hypertonic Saline 7.2%
NDC: 11695-6414 | Form: INJECTION, SOLUTION
Manufacturer: Covetrus
Category: animal | Type: PRESCRIPTION ANIMAL DRUG LABEL
Date: 20190820

ACTIVE INGREDIENTS: SODIUM CHLORIDE 7.2 g/100 mL

Hypertonic saline 7.2%

Indications:

For use in replacement therapy of
sodium, chloride and water which may become
depleted in many diseases.

Caution:

This product contains no preservatives. Use
entire contents when first opened. Discard any
unused solution.

Dosage and Administration:

Warm to body temperature and administer slowly by intravenous or
subcutaneous injection. The amount and rate of
administration must be judged by the veterinarian in
relation to the condition being treated and the clinical
response of the animal, being careful to avoid
overhydration.

GENERAL PRECAUTIONS

Sterile - Preservative Free

FOR ANIMAL USE ONLY

KEEP OUT OF REACH OF CHILDREN

CAUTION:

Federal law restricts this drug to use by or on the order of a licensed veterinarian.

Composition:

Each 100 mL of sterile aqueous
solution contains:
Sodium chloride..........................7.2 g

Milliequivalents per liter

Cations
Sodium.............................1232 mEq/L
Anions
Chloride............................1232 mEq/L

Total osmolarity is 2464 milliosmoles per liter.

STORAGE AND HANDLING

Store between 15°C and 30°C (59°F-86°F)

PRECAUTIONS

TAKE TIME OBSERVE LABEL DIRECTIONS

INFORMATION FOR OWNERS/CAREGIVERS

Reorder #069179

Manufactured by:

Nova-Tech, Inc.

Grand Island, NE 68801

18-806
RMS 92-1178

NDC: 11695-6414-1

Volume: 33.814 fl oz (1000 mL)

Questions? (855) 724-3461

Distributed by:
Covetrus North America

400 Metro Place North

Dublin, OH 43017

covetrus.com

AH-069179-01
Rev: 0719

Lot No. Exp. Date

Assembled in USA